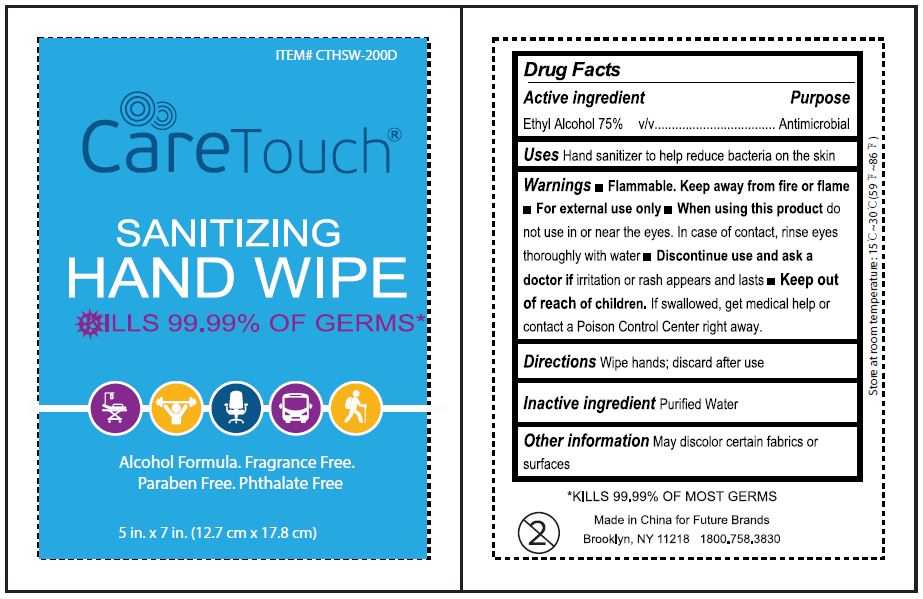 DRUG LABEL: CareTouch Sanitizing Hand wipes
NDC: 79367-001 | Form: LIQUID
Manufacturer: Ningbo Easyclean Commodity Co. Ltd.
Category: otc | Type: HUMAN OTC DRUG LABEL
Date: 20200828

ACTIVE INGREDIENTS: ALCOHOL 75 mL/100 mL
INACTIVE INGREDIENTS: WATER

Active Ingredient

Ethyl Alcohol 75% v/v

Purpose

Antimicrobial

Uses

Hand sanitizer to help reduce bacteria on the skin

Warnings

- Flammable. Keep away from fire or flame.
- For external use only

When using this product do not use in or near the eyes. In case of contact, rinse eyes thoroughly with water

Discontinue use and ask a doctor if irritation or rash appears and lasts

Keep out of reach of children. If swallowed, get medical help or contact a Poison Control Center right away.

Directions

Wipe hands; discard after use

Other Information

May discolor certain fabrics or surfaces

Inactive Ingredients

Purified Water

Package Label/Principal Display Panel

NDC 79367-001-01; 225 mL